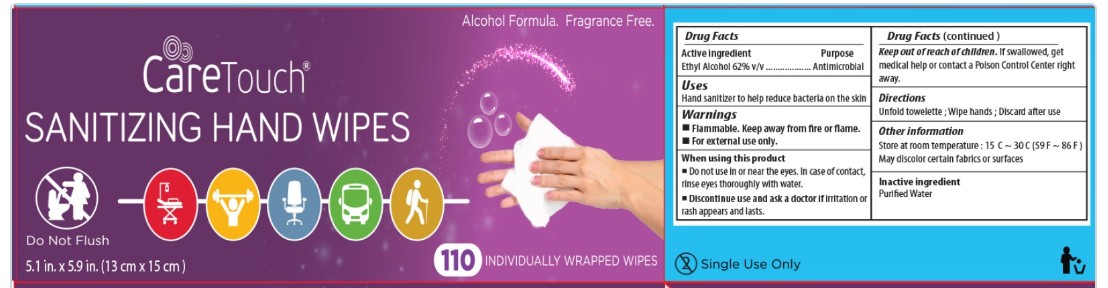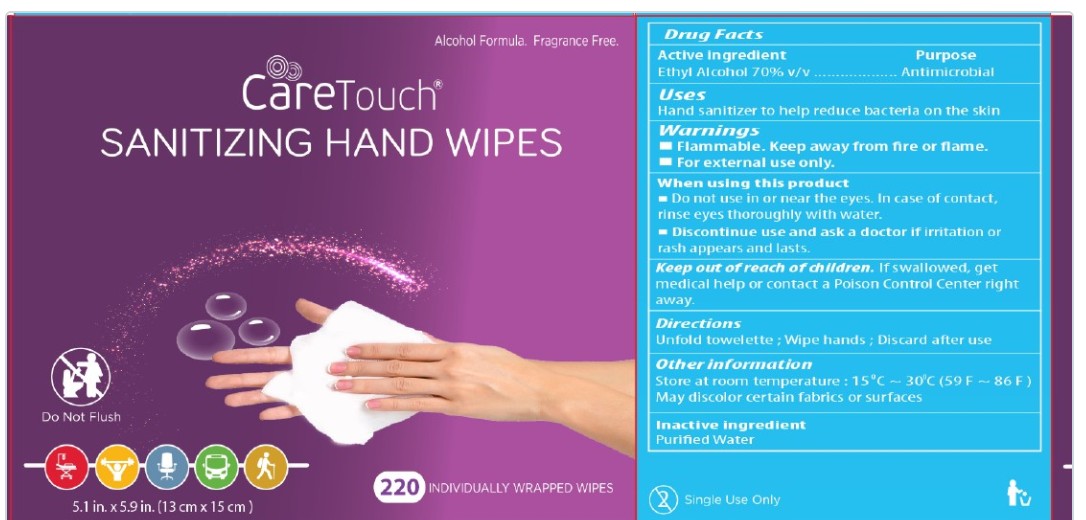 DRUG LABEL: CareTouch
NDC: 60913-026 | Form: CLOTH
Manufacturer: Phoenix Healthcare Solutions LLC
Category: otc | Type: HUMAN OTC DRUG LABEL
Date: 20251023

ACTIVE INGREDIENTS: ALCOHOL 0.62 mL/1 mL
INACTIVE INGREDIENTS: WATER

Care Touch Sanitizing Hand Wipes - Whele LLC

Drug Facts

Active Ingredient

Ethyl Alcohol 62% v/v

Purpose

Antimicrobial

Uses

Hand Sanitizer to help reduce bacteria on the skin

Warnings

Flammable, keep away from Fire or Flame.

For External use only

When using this product

-Do not use in or near the eyes, in case of contact, rinse eyes thoroughly with water

-Discontinue use and ask a doctor if irritation or rash appears and lasts.

Keep out of reach of children. If swallowed, get medical help or contact Poison Control Center right away.

Directions

Unfold towelette, Wipe hands, Discard after use.

Inactive ingredient

Purified Water

Other information

Store at room temperature 15℃ to 30℃

May discolor certain fabrics or surfaces